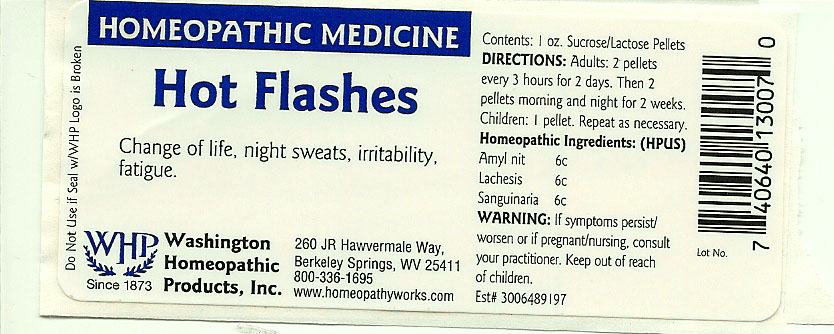 DRUG LABEL: Hot Flashes
NDC: 68428-020 | Form: PELLET
Manufacturer: Washington Homeopathic Products
Category: homeopathic | Type: HUMAN OTC DRUG LABEL
Date: 20191223

ACTIVE INGREDIENTS: AMYL NITRITE 6 [hp_C]/28 g; LACHESIS MUTA VENOM 6 [hp_C]/28 g; SANGUINARIA CANADENSIS ROOT 6 [hp_C]/28 g
INACTIVE INGREDIENTS: SUCROSE; LACTOSE

DRUG FACTS

ACTIVE INGREDIENTS

AMYL NIT 6C

LACHESIS 6C

SANGUINARIA 6C

USES

To relieve the symptoms of change of life, night sweats, irritability, fatigue

KEEP OUT OF REACH OF CHILDREN

Keep this and all medicines out of reach of children.

INDICATIONS

AMYL NIT Anxiety

LACHESIS Sore throat

SANGUINARIA Headache

STOP USE AND ASK DOCTOR

If symptoms persist/worsen or if pregnant/nursing, stop use and consult your practitioner.

DIRECTIONS

Adults 2 pellets every 3 hours for 2 days. Then 2 pellets morning and night for 2 weeks.

Children: 1 pellet. Repeat as necessary.

INACTIVE INGREDIENTS

Sucrose/Lactose

PRINCIPAL DISPLAY PANEL

Enter section text here